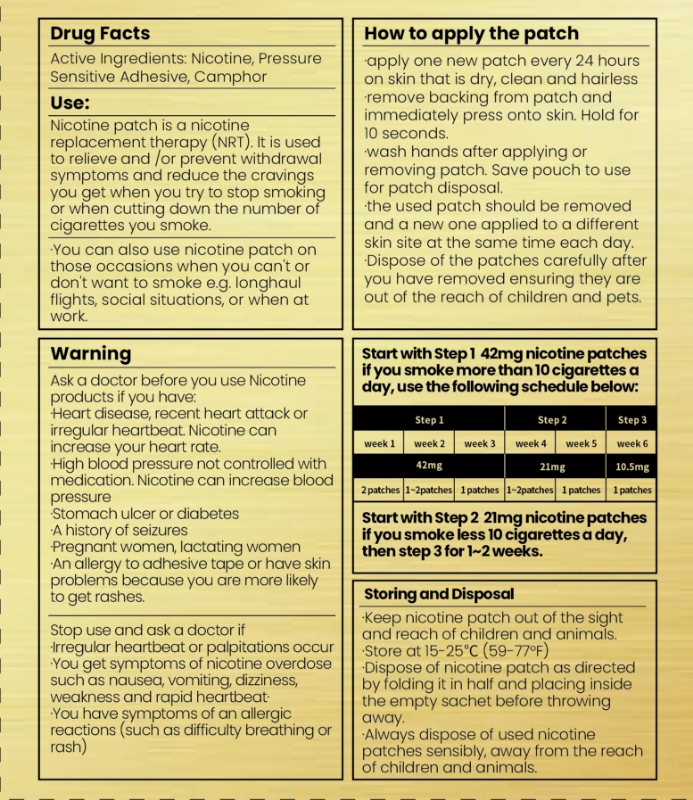 DRUG LABEL: Nicotine Patches
NDC: 85333-002 | Form: PATCH
Manufacturer: Zhejiang FTA Shengzuozhi Biotechnology Co., LTD
Category: otc | Type: HUMAN OTC DRUG LABEL
Date: 20250325

ACTIVE INGREDIENTS: NICOTINE 42 mg/42 mg

ACTIVE INGREDIENT

Nicotine 42mg delivered over 24 hours.......................................................Stop Smoking aid

Nicotine 21mg delivered over 24 hours.......................................................Stop Smoking aid

keep out of reach of children section.

PURPOSE

·apply one new patch every 24 hours on skin that is dry, clean and hairless

·remove backing from patch and immediately press onto skin. Hold for 10 seconds.

·wash hands after applying or removing patch. Save pouch to use for patch disposal.

·the used patch should be removed and a new one applied to a different skin site at the same time each day.

·Dispose of the patches carefully after you have removed ensuring they are out of the reach of children and pets.

keep out of reach of children section

DOSAGE AND ADMINISTRATION

Nicotine 42mg delivered over 24 hours.......................................................Stop Smoking aid

Nicotine 21mg delivered over 24 hours.......................................................Stop Smoking aid

reduces withdrawal symptoms, including nicotine craving, associated with quitting smoking.

INDICATIONS AND USAGE

reduces withdrawal symptoms, including nicotine craving, associated with quitting smoking.

INACTIVE INGREDIENT

Nicotine 42mg

PACKAGE LABEL

reduces withdrawal symptoms, including nicotine craving, associated with quitting smoking.